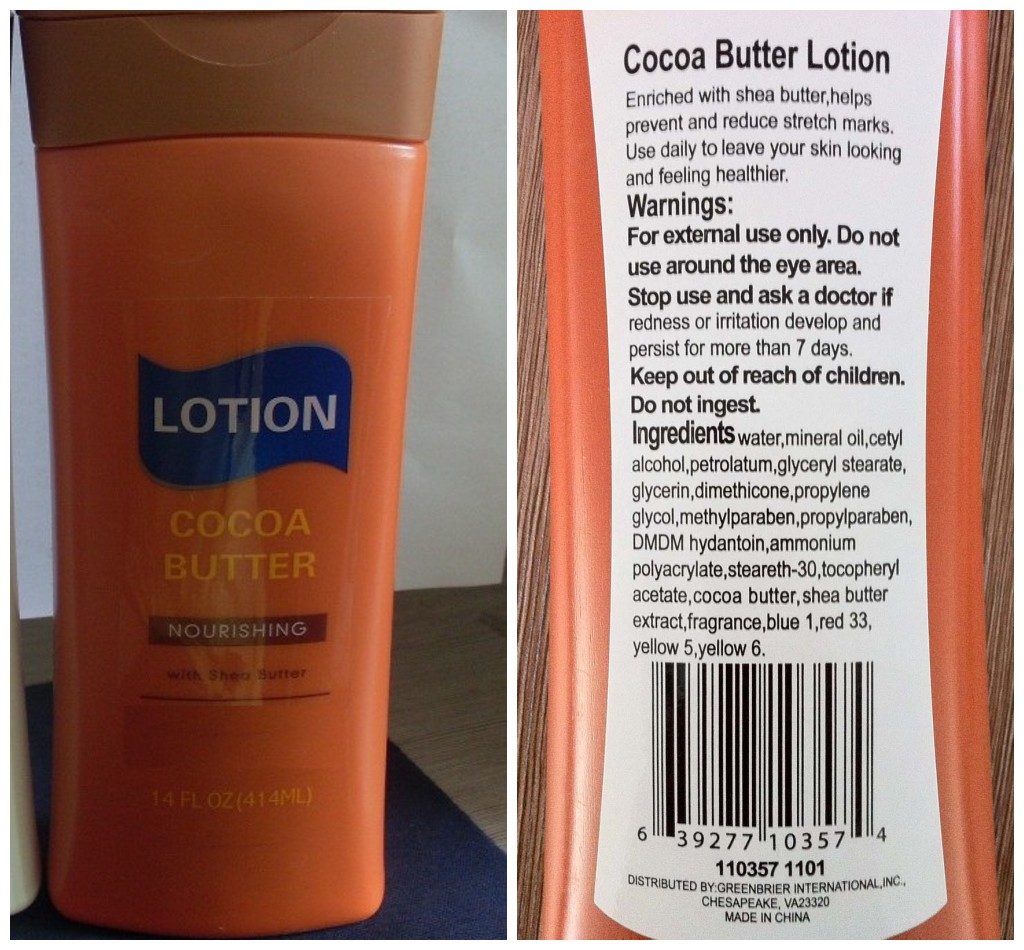 DRUG LABEL: Cocoa Butter
NDC: 33992-1108 | Form: LOTION
Manufacturer: GREENBRIER INTERNATIONAL
Category: otc | Type: HUMAN OTC DRUG LABEL
Date: 20110802

ACTIVE INGREDIENTS: petrolatum  5 g/100 g
INACTIVE INGREDIENTS: water; mineral oil; cetyl alcohol; GLYCERYL MONOSTEARATE; glycerin; dimethicone; propylene glycol; methylparaben; propylparaben; steareth-30; cocoa butter; FD&C BLUE NO. 1; D&C RED NO. 33; FD&C YELLOW NO. 5; FD&C YELLOW NO. 6

Drug Facts

Active Ingredient Purpose

Petrolatum 5% Skin Protectant

PURPOSE

Skin Protectant

Keep out of reach of children

INDICATIONS AND USAGE

Use daily, do not use around eye area

WARNINGS

For external use only, Do not use around the eye area.Stop use and ask a doctor if redness or imitation develop and persist for more than 7 days

DOSAGE AND ADMINISTRATION

apply as needed

INACTIVE INGREDIENT

water, mineral oil, cetyl alcohol, glyceryl stearate, glycerin, dimethicone, propylene glycol, methylparaben, propylparaben, DMDM hydantoin, ammonium polyacrylate, steareth-30, tocopheryl acetate, cocoa butter, shea butter extract, fragrance, blue 1, red 33, yellow 5, yellow 6